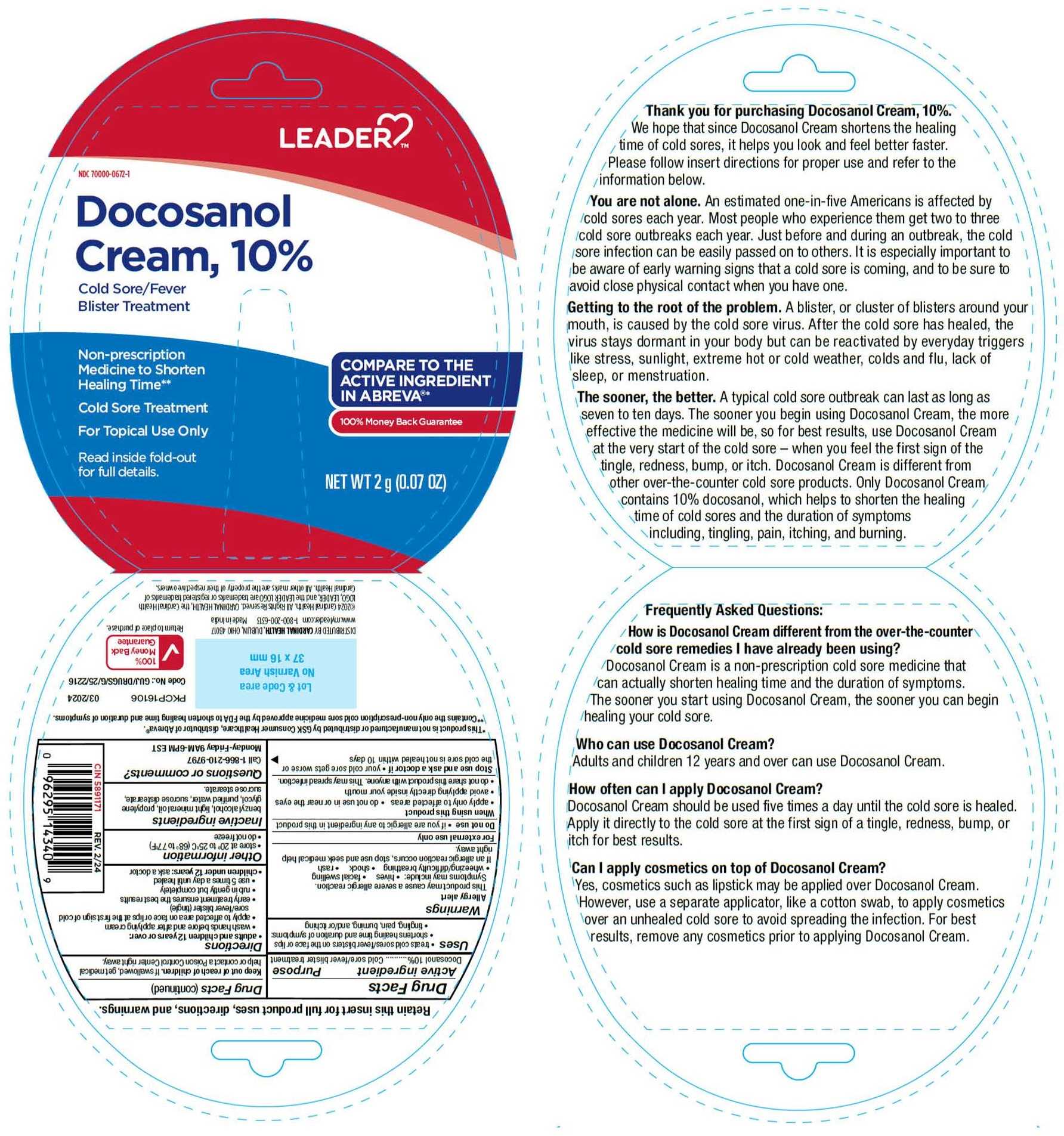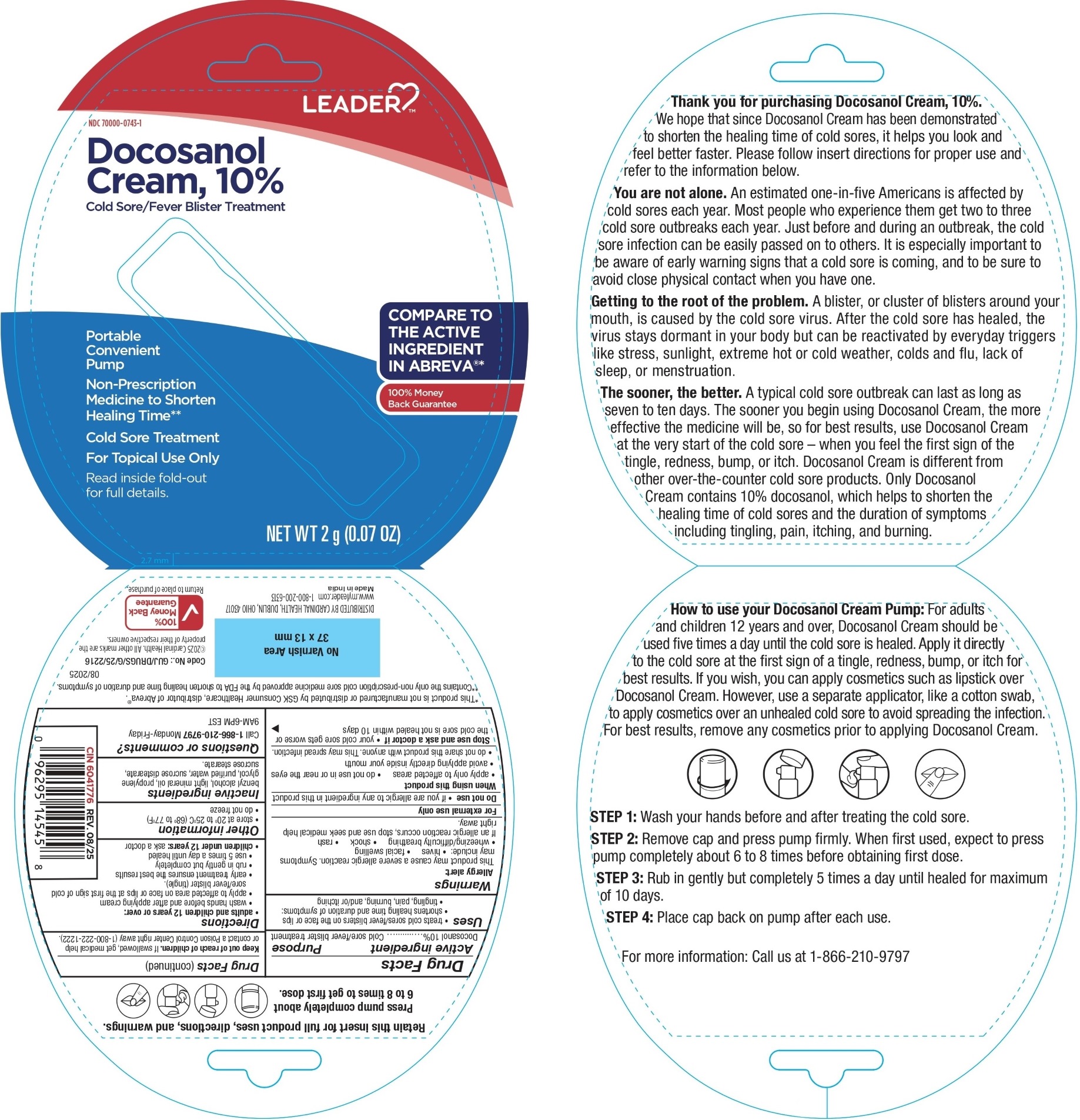 DRUG LABEL: Docosanol
NDC: 70000-0672 | Form: CREAM
Manufacturer: Leader/ Cardinal Health 110, Inc.
Category: otc | Type: HUMAN OTC DRUG LABEL
Date: 20251225

ACTIVE INGREDIENTS: DOCOSANOL 100 mg/1 g
INACTIVE INGREDIENTS: BENZYL ALCOHOL; LIGHT MINERAL OIL; PROPYLENE GLYCOL; WATER; SUCROSE DISTEARATE; SUCROSE STEARATE

Docosanol Cream, 10%

Active Ingredient

Docosanol 10%

Purpose

Cold sore/fever blister treatment

Uses

- treats cold sores/fever blisters on the face or lips
- shortens healing time and duration of symptoms:

• tingling, pain, burning, and/or itching

Warnings

Allergy Alert

This product may cause a severe allergic reaction. Symptoms may include:

- hives
- facial swelling
- wheezing/difficulty breathing
- shock
- rash

If an allergic reaction occurs, stop use and seek medical help right away.

For external use only

Do not use

- if you are allergic to any ingredient in this produc

When using this product

- apply only to the affected areas
- do not use in or near the eyes
- avoid applying directly inside your mouth
- do not share this product with anyone. This may spread the infection.

Stop use and ask a doctor if

- your cold sore gets worse or the cold sore is not healed within 10 days

Keep out of reach of children

If swallowed, get medical help or contact a Poison Control Center right away.

Directions

- adults and children 12 years or over:

• wash hands before and after applying cream

• apply to affected area on the face or lips at the first sign of cold sore/fever blister (tingle)

• early treatment ensures the best results

• rub in gently but completely

• use 5 times a day until healed

- children under 12 years: ask a doctor

Other information

- store at 20° to 25°C (68° to 77°F)
- do not freeze

Inactive ingredients

benzyl alcohol, light mineral oil, propylene glycol, purified water, sucrose distearate, sucrose stearate

Questions or comments?

Call 1-866-210-9797 Monday-Friday 9AM-6PM EST

PRINCIPAL DISPLAY PANEL

TUBE PACK

NDC 70000-0672-1

Docosanol Cream, 10%

Compare to the active ingredient in Abreva®*

Cold Sore/Fever Blister Treatment

Non-prescription Medicine to Shorten Healing Time**

Cold Sore Treatment

For Topical Use Only

NET WT 2g (0.07 oz)

*This product is not manufactured or distributed by GSK Consumer Healthcare, distributor of Abreva®.

**Contains the only non-prescription cold sore medicine approved by the FDA to shorten healing time and duration of symptoms.

RETAIN THIS INSERT FOR FULL PRODUCT USES, DIRECTIONS AND WARNINGS

Distributed by:

CARDINAL HEALTH,

DUBLIN, OHIO 43017

Code No.: GUJ/DRUGS/G/25/2216

Made in India

PUMP PACK

NDC 70000-0743-1

Docosanol Cream, 10%

Compare to the active ingredient in Abreva®*

Cold Sore/Fever Blister Treatment

Non-Prescription Medicine to Shorten Healing Time**

Cold Sore Treatment

For Topical Use Only

NET WT 2g (0.07 oz)

*This product is not manufactured or distributed by GSK Consumer Healthcare, distributor of Abreva®.

**Contains the only non-prescription cold sore medicine approved by the FDA to shorten healing time and duration of symptoms.

RETAIN THIS INSERT FOR FULL PRODUCT USES, DIRECTIONS AND WARNINGS

Distributed by:

CARDINAL HEALTH,

DUBLIN, OHIO 43017

Code No.: GUJ/DRUGS/G/25/2216

Made in India